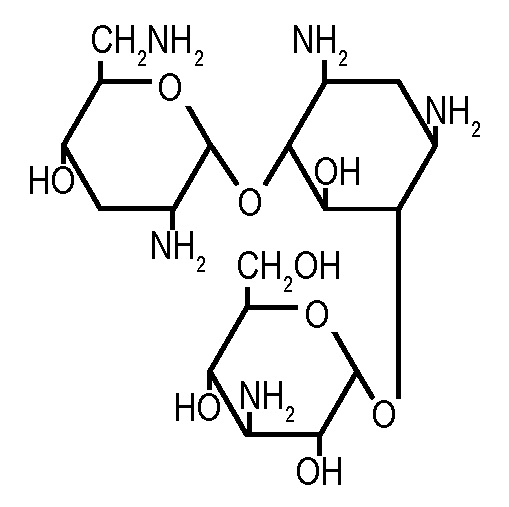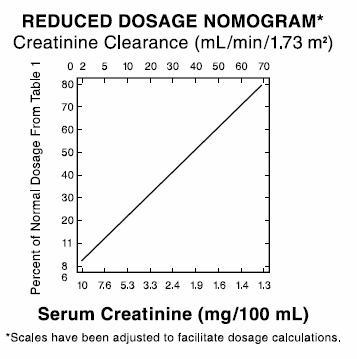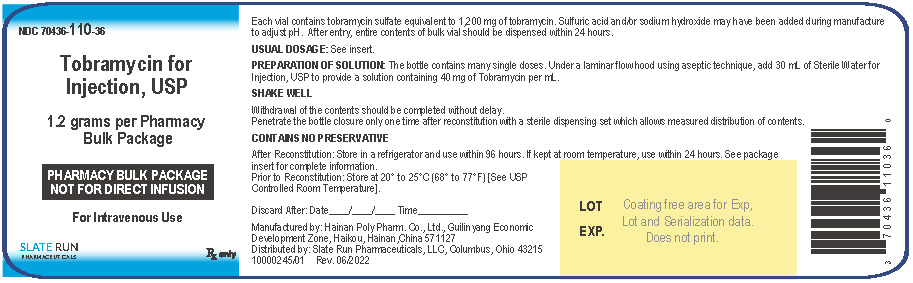 DRUG LABEL: tobramycin
NDC: 70436-110 | Form: INJECTION, POWDER, FOR SOLUTION
Manufacturer: Slate Run Pharmaceuticals, LLC
Category: prescription | Type: HUMAN PRESCRIPTION DRUG LABEL
Date: 20260210

ACTIVE INGREDIENTS: TOBRAMYCIN 1200 mg/30 mL

Tobramycin for Injection, USP

Rx only

PHARMACY BULK PACKAGE – NOT FOR DIRECT INFUSION

To reduce the development of drug-resistant bacteria and maintain the effectiveness of tobramycin and other antibacterial drugs, tobramycin should be used only to treat or prevent infections that are proven or strongly suspected to be caused by bacteria.

WARNINGS

Patients treated with Tobramycin for Injection, USP and other aminoglycosides should be under close clinical observation, because these drugs have an inherent potential for causing ototoxicity and nephrotoxicity.

Neurotoxicity, manifested as both auditory and vestibular ototoxicity, can occur. The auditory changes are irreversible, are usually bilateral, and may be partial or total. Eighth-nerve impairment and nephrotoxicity may develop, primarily in patients having preexisting renal damage and in those with normal renal function to whom aminoglycosides are administered for longer periods or in higher doses than those recommended. Other manifestations of neurotoxicity may include numbness, skin tingling, muscle twitching, and convulsions. The risk of aminoglycoside-induced hearing loss increases with the degree of exposure to either high peak or high trough serum concentrations. Patients who develop cochlear damage may not have symptoms during therapy to warn them of eighth-nerve toxicity, and partial or total irreversible bilateral deafness may continue to develop after the drug has been discontinued. Rarely, nephrotoxicity may not become apparent until the first few days after cessation of therapy. Aminoglycoside-induced nephrotoxicity usually is reversible.

Renal and eighth-nerve function should be closely monitored in patients with known or suspected renal impairment and also in those whose renal function is initially normal but who develop signs of renal dysfunction during therapy. Peak and trough serum concentrations of aminoglycosides should be monitored periodically during therapy to assure adequate levels and to avoid potentially toxic levels. Prolonged serum concentrations above 12 mcg/mL should be avoided. Rising trough levels (above 2 mcg/mL) may indicate tissue accumulation. Such accumulation, excessive peak concentrations, advanced age, and cumulative dose may contribute to ototoxicity and nephrotoxicity (see PRECAUTIONS). Urine should be examined for decreased specific gravity and increased excretion of protein, cells, and casts. Blood urea nitrogen, serum creatinine, and creatinine clearance should be measured periodically. When feasible, it is recommended that serial audiograms be obtained in patients old enough to be tested, particularly high-risk patients. Evidence of impairment of renal, vestibular, or auditory function requires discontinuation of the drug or dosage adjustment.

Tobramycin should be used with caution in premature and neonatal infants because of their renal immaturity and the resulting prolongation of serum half-life of the drug.

Concurrent and sequential use of other neurotoxic and/or nephrotoxic antibiotics, particularly other aminoglycosides (e.g., amikacin, streptomycin, neomycin, kanamycin, gentamicin, and paromomycin), cephaloridine, viomycin, polymyxin B, colistin, cisplatin, and vancomycin, should be avoided. Other factors that may increase patient risk are advanced age and dehydration.

Aminoglycosides should not be given concurrently with potent diuretics, such as ethacrynic acid and furosemide. Some diuretics themselves cause ototoxicity, and intravenously administered diuretics enhance aminoglycoside toxicity by altering antibiotic concentrations in serum and tissue.

Aminoglycosides can cause fetal harm when administered to a pregnant woman (see PRECAUTIONS).

DESCRIPTION

Tobramycin sulfate, a water-soluble antibiotic of the aminoglycoside group, is derived from the actinomycete Streptomyces tenebrarius. Tobramycin for Injection, USP is a white or off-white lyophilized porous cake for parenteral administration.

Each vial contains tobramycin sulfate equivalent to 1200 mg of tobramycin; After reconstitution, each mL contains 40 mg of tobramycin, contains sulfuric acid and may contain sodium hydroxide for pH adjustment.

Tobramycin sulfate is O-3-amino-3-deoxy-α-D-glucopyranosyl-(1→4)- O-[2,6-diamino-2,3,6-trideoxy-α-D- ribo-hexopyranosyl-(1→6)]-2-deoxy-L-streptamine, (2:5)(salt) and has the chemical formula (C18H37N5O9)2•5H2SO4. The molecular weight is 1,425.39. The structural formula for tobramycin is as follows:

A pharmacy bulk package is a container of a sterile preparation for parenteral use that contains many single doses. The contents are intended for use in a pharmacy admixture service and are restricted to the preparation of admixtures for intravenous infusion (see DOSAGE AND ADMINISTRATION: Directions for proper use of Pharmacy Bulk Package).

CLINICAL PHARMACOLOGY

Tobramycin is rapidly absorbed following intramuscular administration. Peak serum concentrations of tobramycin occur between 30 and 90 minutes after intramuscular administration.

Following an intramuscular dose of 1 mg/kg of body weight, maximum serum concentrations reach about 4 mcg/mL, and measurable levels persist for as long as 8 hours. Therapeutic serum levels are generally considered to range from 4 to 6 mcg/mL. When tobramycin sulfate is administered by intravenous infusion over a 1-hour period, the serum concentrations are similar to those obtained by intramuscular administration. Tobramycin is poorly absorbed from the gastrointestinal tract.

In patients with normal renal function, except neonates, tobramycin administered every 8 hours does not accumulate in the serum. However, in those patients with reduced renal function and in neonates, the serum concentration of the antibiotic is usually higher and can be measured for longer periods of time than in normal adults. Dosage for such patients must, therefore, be adjusted accordingly (see DOSAGE AND ADMINISTRATION).

Following parenteral administration, little, if any, metabolic transformation occurs, and tobramycin is eliminated almost exclusively by glomerular filtration. Renal clearance is similar to that of endogenous creatinine. Ultrafiltration studies demonstrate that practically no serum protein binding occurs. In patients with normal renal function, up to 84% of the dose is recoverable from urine in 8 hours and up to 93% in 24 hours.

Peak urine concentrations ranging from 75 to 100 mcg/mL have been observed following the intramuscular injection of a single dose of 1 mg/kg. After several days of treatment, the amount of tobramycin excreted in the urine approaches the daily dose administered. When renal function is impaired, excretion of tobramycin is slowed, and accumulation of the drug may cause toxic blood levels.

The serum half-life in normal individuals is 2 hours. An inverse relationship exists between serum half-life and creatinine clearance, and the dosage schedule should be adjusted according to the degree of renal impairment (see DOSAGE AND ADMINISTRATION). In patients undergoing dialysis, 25% to 70% of the administered dose may be removed, depending on the duration and type of dialysis.

Tobramycin can be detected in tissues and body fluids after parenteral administration. Concentrations in bile and stools ordinarily have been low, which suggests minimum biliary excretion. Tobramycin has appeared in low concentration in the cerebrospinal fluid following parenteral administration, and concentrations are dependent on dose, rate of penetration, and degree of meningeal inflammation. It has also been found in sputum, peritoneal fluid, synovial fluid, and abscess fluids, and it crosses the placental membranes. Concentrations in the renal cortex are several times higher than the usual serum levels.

Probenecid does not affect the renal tubular transport of tobramycin.

Microbiology

Tobramycin is an aminoglycoside antibiotic with activity against Gram-positive and Gram-negative bacteria.

Mechanism of Action

Tobramycin acts by inhibiting synthesis of protein in bacterial cells. In vitrotests demonstrate that tobramycin is bactericidal.

Interactions with Other Antibiotics

Although most strains of enterococci demonstrate in vitroresistance, some strains in this group are susceptible. In vitrostudies have shown that an aminoglycoside combined with an antibiotic that interferes with cell-wall synthesis affects some enterococcal strains synergistically. The combination of penicillin G and tobramycin results in a synergistic bactericidal effect in vitroagainst certain strains of Enterococcus faecalis. However, this combination is not synergistic against other closely related organisms, e.g. Enterococcus faecium. Speciation of enterococci alone cannot be used to predict susceptibility. Susceptibility testing and tests for antibiotic synergism are emphasized.

Cross-Resistance

Cross-resistance between aminoglycosides may occur.

Tobramycin has been shown to be active against most strains of the following organisms both in vitroand in clinical infections: (see INDICATIONS AND USAGE)

Aerobic and facultative Gram-positive microorganisms

Staphylococcus aureus

Aerobic and facultative Gram-negative microorganisms

Citrobactersp

Enterobactersp

Escherichia coli

Klebsiellasp

Morganella morganii

Pseudomonas aeruginosa

Proteus mirabilis

Proteus vulgaris

Providenciasp

Serratiasp

Aminoglycosides have a low order of activity against most Gram-positive organisms, including Streptococcus pyogenes, Streptococcus pneumoniae, and enterococci.

Susceptibility Tests

For specific information regarding susceptibility test interpretive criteria and associated test methods and quality control standards recognized by FDA for this drug, please see: https://www.fda.gov/STIC.

INDICATIONS AND USAGE

Tobramycin is indicated for the treatment of serious bacterial infections caused by susceptible strains of the designated microorganisms in the diseases listed below:

Septicemia in the neonate, child, and adult caused by P. aeruginosa, E. coli, and Klebsiellasp.

Lower respiratory tract infections caused by P. aeruginosa, Klebsiellasp, Enterobactersp, Serratiasp, E. coli, and S. aureus(penicillinase and non-penicillinase-producing strains).

Serious central-nervous-system infections (meningitis) caused by susceptible organisms.

Intra-abdominal infections, including peritonitis, caused by E. coli, Klebsiellasp, and Enterobactersp.

Skin, bone, and skin structure infections caused by P. aeruginosa, Proteussp, E. coli, Klebsiellasp, Enterobactersp, and S. aureus.

Complicated and recurrent urinary tract infections caused by P. aeruginosa, Proteussp (indole-positive and indole-negative), E. coli, Klebsiellasp, Enterobactersp, Serratiasp, S. aureus, Providenciasp, and Citrobactersp.

Aminoglycosides, including tobramycin sulfate, are not indicated in uncomplicated initial episodes of urinary tract infections unless the causative organisms are not susceptible to antibiotics having less potential toxicity. Tobramycin may be considered in serious staphylococcal infections when penicillin or other potentially less toxic drugs are contraindicated and when bacterial susceptibility testing and clinical judgment indicate its use.

Bacterial cultures should be obtained prior to and during treatment to isolate and identify etiologic organisms and to test their susceptibility to tobramycin. If susceptibility tests show that the causative organisms are resistant to tobramycin, other appropriate therapy should be instituted. In patients in whom a serious life-threatening gram-negative infection is suspected, including those in whom concurrent therapy with a penicillin or cephalosporin and an aminoglycoside may be indicated, treatment with tobramycin sulfate may be initiated before the results of susceptibility studies are obtained. The decision to continue therapy with tobramycin should be based on the results of susceptibility studies, the severity of the infection, and the important additional concepts discussed in the WARNINGSbox above.

To reduce the development of drug-resistant bacteria and maintain the effectiveness of tobramycin and other antibacterial drugs, tobramycin should be used only to treat or prevent infections that are proven or strongly suspected to be caused by susceptible bacteria. When culture and susceptibility information are available, they should be considered in selecting or modifying antibacterial therapy. In the absence of such data, local epidemiology and susceptibility patterns may contribute to the empiric selection of therapy.

CONTRAINDICATIONS

A hypersensitivity to any aminoglycoside is a contraindication to the use of tobramycin. A history of hypersensitivity or serious toxic reactions to aminoglycosides may also contraindicate the use of any other aminoglycoside because of the known cross-sensitivity of patients to drugs in this class.

WARNINGS

See WARNINGSbox above.

This product contains sodium metabisulfite, a sulfite that may cause allergic-type reactions, including anaphylactic symptoms and life-threatening or less severe asthmatic episodes, in certain susceptible people. The overall prevalence of sulfite sensitivity in the general population is unknown and probably low. Sulfite sensitivity is seen more frequently in asthmatic than in nonasthmatic people.

Serious allergic reactions including anaphylaxis and dermatologic reactions including exfoliative dermatitis, toxic epidermal necrolysis, erythema multiforme, and Stevens Johnson Syndrome have been reported rarely in patients on tobramycin therapy. Although rare, fatalities have been reported. (See CONTRAINDICATIONS).

If an allergic reaction occurs, the drug should be discontinued and appropriate therapy instituted.

Clostridium difficileassociated diarrhea (CDAD) has been reported with use of nearly all antibacterial agents, including tobramycin, and may range in severity from mild diarrhea to fatal colitis. Treatment with antibacterial agents alters the normal flora of the colon leading to overgrowth of C. difficile.

C. difficileproduces toxins A and B which contribute to the development of CDAD. Hypertoxin producing strains of C. difficilecause increased morbidity and mortality, as these infections can be refractory to antimicrobial therapy and may require colectomy. CDAD must be considered in all patients who present with diarrhea following antibiotic use. Careful medical history is necessary since CDAD has been reported to occur over two months after the administration of antibacterial agents.

If CDAD is suspected or confirmed, ongoing antibiotic use not directed against C. difficilemay need to be discontinued. Appropriate fluid and electrolyte management, protein supplementation, antibiotic treatment of C. difficile, and surgical evaluation should be instituted as clinically indicated.

PRECAUTIONS

General

Prescribing tobramycin in the absence of a proven or strongly suspected bacterial infection or a prophylactic indication is unlikely to provide benefit to the patient and increases the risk of the development of drug-resistant bacteria.

Serum and urine specimens for examination should be collected during therapy, as recommended in the WARNINGSbox. Serum calcium, magnesium, and sodium should be monitored.

Peak and trough serum levels should be measured periodically during therapy. Prolonged concentrations above 12 mcg/mL should be avoided. Rising trough levels (above 2 mcg/mL) may indicate tissue accumulation. Such accumulation, advanced age, and cumulative dosage may contribute to ototoxicity and nephrotoxicity. It is particularly important to monitor serum levels closely in patients with known renal impairment.

A useful guideline would be to perform serum level assays after 2 or 3 doses, so that the dosage could be adjusted if necessary, and at 3- to 4-day intervals during therapy. In the event of changing renal function, more frequent serum levels should be obtained and the dosage or the dosage interval adjusted according to the guidelines provided in the DOSAGE AND ADMINISTRATIONsection.

In order to measure the peak level, a serum sample should be drawn about 30 minutes following intravenous infusion or 1 hour after an intramuscular injection. Trough levels are measured by obtaining serum samples at 8 hours or just prior to the next dose of tobramycin. These suggested time intervals are intended only as guidelines and may vary according to institutional practices. It is important, however, that there be consistency within the individual patient program unless computerized pharmacokinetic dosing programs are available in the institution. These serum-level assays may be especially useful for monitoring the treatment of severely ill patients with changing renal function or of those infected with less susceptible organisms or those receiving maximum dosage.

Neuromuscular blockade and respiratory paralysis have been reported in cats receiving very high doses of tobramycin (40 mg/kg). The possibility of prolonged or secondary apnea should be considered if tobramycin is administered to anesthetized patients who are also receiving neuromuscular blocking agents, such as succinylcholine, tubocurarine, or decamethonium, or to patients receiving massive transfusions of citrated blood. If neuromuscular blockade occurs, it may be reversed by the administration of calcium salts.

Cross-allergenicity among aminoglycosides has been demonstrated.

In patients with extensive burns, altered pharmacokinetics may result in reduced serum concentrations of aminoglycosides. In such patients treated with tobramycin, measurement of serum concentration is especially important as a basis for determination of appropriate dosage.

Elderly patients may have reduced renal function that may not be evident in the results of routine screening tests, such as BUN or serum creatinine. A creatinine clearance determination may be more useful. Monitoring of renal function during treatment with aminoglycosides is particularly important in such patients.

An increased incidence of nephrotoxicity has been reported following concomitant administration of aminoglycoside antibiotics and cephalosporins.

Aminoglycosides should be used with caution in patients with muscular disorders, such as myasthenia gravis or parkinsonism, since these drugs may aggravate muscle weakness because of their potential curare-like effect on neuromuscular function.

Aminoglycosides may be absorbed in significant quantities from body surfaces after local irrigation or application and may cause neurotoxicity and nephrotoxicity.

Aminoglycosides have not been approved for intraocular and/or subconjunctival use. Physicians are advised that macular necrosis has been reported following administration of aminoglycosides, including tobramycin, by these routes.

See WARNINGSbox regarding concurrent use of potent diuretics and concurrent and sequential use of other neurotoxic or nephrotoxic drugs.

The inactivation of tobramycin and other aminoglycosides by β-lactam-type antibiotics (penicillins or cephalosporins) has been demonstrated in vitroand in patients with severe renal impairment. Such inactivation has not been found in patients with normal renal function who have been given the drugs by separate routes of administration.

Therapy with tobramycin may result in overgrowth of nonsusceptible organisms. If overgrowth of nonsusceptible organisms occurs, appropriate therapy should be initiated.

Aminoglycosides can cause fetal harm when administered to a pregnant woman. Aminoglycoside antibiotics cross the placenta, and there have been several reports of total irreversible bilateral congenital deafness in children whose mothers received streptomycin during pregnancy. Serious side effects to mother, fetus, or newborn have not been reported in the treatment of pregnant women with other aminoglycosides. If tobramycin is used during pregnancy or if the patient becomes pregnant while taking tobramycin, she should be apprised of the potential hazard to the fetus.

Pediatric Use

See INDICATIONS AND USAGEand DOSAGE AND ADMINISTRATION.

Geriatric Use

Elderly patients may be at a higher risk of developing nephrotoxicity and ototoxicity while receiving tobramycin (see WARNINGS, PRECAUTIONS, and OVERDOSAGE). Other factors that may contribute to nephrotoxicity and ototoxicity are rising trough levels, excessive peak concentrations, dehydration, concomitant use of other neurotoxic or nephrotoxic drugs, and cumulative dose. Peak and trough serum levels should be measured periodically during therapy to assure adequate levels and to avoid potentially toxic levels (see WARNINGSand PRECAUTIONS). Tobramycin is known to be substantially excreted by the kidney, and the risk of toxic reactions to this drug may be greater in patients with impaired renal function. Dose reduction is required for patients with impaired renal function (see DOSAGE AND ADMINISTRATION). Elderly patients may have reduced renal function that may not be evident in the results of routine screening tests, such as BUN or serum creatinine. A creatinine clearance determination may be more useful. Monitoring of renal function during treatment with aminoglycosides is particularly important in the elderly (see PRECAUTIONS).

Tobramycin 40 mg/mL in 50 mL Pharmacy Bulk Package vial contains 35.995 mg (1.565 mEq) of sodium.

Information for Patients

Patients should be counseled that antibacterial drugs including tobramycin should only be used to treat bacterial infections. They do not treat viral infections (e.g., the common cold). When an antibacterial drug product is prescribed to treat a bacterial infection, patients should be told that although it is common to feel better early in the course of therapy, the medication should be taken exactly as directed. Skipping doses or not completing the full course of therapy may (1) decrease the effectiveness of the immediate treatment and (2) increase the likelihood that bacteria will develop resistance and will not be treatable by tobramycin or other antibacterial drugs in the future.

Diarrhea is a common problem caused by antibiotics, which usually ends when the antibiotic is discontinued. Sometimes after starting treatment with antibiotics, patients can develop watery and bloody stools (with or without stomach cramps and fever) even as late as two or more months after having taken the last dose of the antibiotic. If this occurs, patients should contact their physician as soon as possible.

ADVERSE REACTIONS

Neurotoxicity

Adverse effects on both the vestibular and auditory branches of the eighth nerve have been noted, especially in patients receiving high doses or prolonged therapy, in those given previous courses of therapy with an ototoxin, and in cases of dehydration. Symptoms include dizziness, vertigo, tinnitus, roaring in the ears, and hearing loss. Hearing loss is usually irreversible and is manifested initially by diminution of high-tone acuity. Tobramycin and gentamicin sulfates closely parallel each other in regard to ototoxic potential.

Nephrotoxicity

Renal function changes, as shown by rising BUN, NPN, and serum creatinine and by oliguria, cylindruria, and increased proteinuria, have been reported, especially in patients with a history of renal impairment who are treated for longer periods or with higher doses than those recommended. Adverse renal effects can occur in patients with initially normal renal function.

Clinical studies and studies in experimental animals have been conducted to compare the nephrotoxic potential of tobramycin and gentamicin. In some of the clinical studies and in the animal studies, tobramycin caused nephrotoxicity significantly less frequently than gentamicin. In some other clinical studies, no significant difference in the incidence of nephrotoxicity between tobramycin and gentamicin was found.

Other reported adverse reactions possibly related to tobramycin sulfate include anemia, granulocytopenia, and thrombocytopenia; and fever, rash, exfoliative dermatitis, itching, urticaria, nausea, vomiting, diarrhea, headache, lethargy, pain at the injection site, mental confusion, and disorientation. Laboratory abnormalities possibly related to tobramycin include increased serum transaminases (SGOT, SGPT); increased serum LDH and bilirubin; decreased serum calcium, magnesium, sodium, and potassium; and leukopenia, leukocytosis, and eosinophilia.

OVERDOSAGE

Signs and Symptoms

The severity of the signs and symptoms following a tobramycin overdose are dependent on the dose administered, the patient’s renal function, state of hydration, and age and whether or not other medications with similar toxicities are being administered concurrently. Toxicity may occur in patients treated more than 10 days, in adults given more than 5 mg/kg/day, children given more than 7.5 mg/kg/day, or patients with reduced renal function whose dose has not been appropriately adjusted.

Nephrotoxicity following the parenteral administration of an aminoglycoside is most closely related to the area under the curve of the serum concentration versus time graph. Nephrotoxicity is more likely if trough blood concentrations fail to fall below 2 mcg/mL and is also proportional to the average blood concentration. Patients who are elderly, have abnormal renal function, are receiving other nephrotoxic drugs, or are volume depleted are at greater risk for developing acute tubular necrosis. Auditory and vestibular toxicity has been associated with aminoglycoside overdose; these toxicities occur in patients treated longer than 10 days, in patients with abnormal renal function, in dehydrated patients, or in patients receiving medications with additive auditory toxicities. These patients may not have signs or symptoms or may experience dizziness, tinnitus, vertigo, and a loss of high-tone acuity as ototoxicity progresses. Ototoxicity signs and symptoms may not begin to occur until long after the drug has been discontinued.

Neuromuscular blockade or respiratory paralysis may occur following administration of many aminoglycosides. Neuromuscular blockade, respiratory failure, and prolonged respiratory paralysis may occur more commonly in patients with myasthenia gravis or Parkinson’s disease. Prolonged respiratory paralysis may also occur in patients receiving decamethonium, tubocurarine, or succinylcholine. If neuromuscular blockade occurs, it may be reversed by the administration of calcium salts but mechanical assistance may be necessary.

If tobramycin were ingested, toxicity would be less likely because aminoglycosides are poorly absorbed from an intact gastrointestinal tract.

Treatment

In all cases of suspected overdosage, call your Regional Poison Control Center to obtain the most up-to-date information about the treatment of overdose. This recommendation is made because, in general, information regarding the treatment of overdose may change more rapidly than the package insert. In managing overdosage, consider the possibility of multiple drug overdoses, interaction among drugs, and unusual drug kinetics in your patient.

The initial intervention in a tobramycin overdose is to establish an airway and ensure oxygenation and ventilation. Resuscitative measures should be initiated promptly if respiratory paralysis occurs.

Patients that have received an overdose of tobramycin and who have normal renal function should be adequately hydrated to maintain a urine output of 3 to 5 mL/kg/hr. Fluid balance, creatinine clearance, and tobramycin plasma levels should be carefully monitored until the serum tobramycin level falls below 2 mcg/mL.

Patients in whom the elimination half-life is greater than 2 hours or whose renal function is abnormal may require more aggressive therapy. In such patients, hemodialysis may be beneficial.

DOSAGE AND ADMINISTRATION

Tobramycin for Injection, USP may be given intramuscularly or intravenously. Recommended dosages are the same for both routes. This insert is for a Pharmacy Bulk Package and is intended for preparing I.V. admixtures only. Dosage recommendations for intramuscular use are for informational purposes only. The patient’s pretreatment body weight should be obtained for calculation of correct dosage. It is desirable to measure both peak and trough serum concentrations (see WARNINGSbox and PRECAUTIONS).

Administration for Patients with Normal Renal Function

Adults With Serious Infections

3 mg/kg/day in 3 equal doses every 8 hours (see Table 3).

Adults With Life-Threatening Infections

Up to 5 mg/kg/day may be administered in 3 or 4 equal doses (see Table 3). The dosage should be reduced to 3 mg/kg/day as soon as clinically indicated. To prevent increased toxicity due to excessive blood levels, dosage should not exceed 5 mg/kg/day unless serum levels are monitored (see WARNINGSbox and PRECAUTIONS).

Table 1: Dosage Schedule Guide for Tobramycin for Injection, USP in Adults with Normal Renal Function (Dosage at 8-Hour Intervals)
For Patient Weighing |  | Usual Dose for Serious Infection |  |  | Maximum Dose for Life-Threatening Infections (Reduce as soon as possible)
kg | lb | 1 mg/kg q8h (Total, 3 mg/kg/day) |  |  | 1.66 mg/kg q8h (Total, 5 mg/kg/day)
 |  | mg/dose | q8h | mL/dose [Applicable to all product forms except Tobramycin Injection, USP, 10 mg/mL (Pediatric)] | mg/dose | q8h | mL/dose
120 | 264 | 120 mg |  | 3 mL | 200 mg |  | 5 mL
115 | 253 | 115 mg |  | 2.9 mL | 191 mg |  | 4.75 mL
110 | 242 | 110 mg |  | 2.75 mL | 183 mg |  | 4.5 mL
105 | 231 | 105 mg |  | 2.6 mL | 175 mg |  | 4.4 mL
100 | 220 | 100 mg |  | 2.5 mL | 166 mg |  | 4.2 mL
95 | 209 | 95 mg |  | 2.4 mL | 158 mg |  | 4 mL
90 | 198 | 90 mg |  | 2.25 mL | 150 mg |  | 3.75 mL
85 | 187 | 85 mg |  | 2.1 mL | 141 mg |  | 3.5 mL
80 | 176 | 80 mg |  | 2 mL | 133 mg |  | 3.3 mL
75 | 165 | 75 mg |  | 1.9 mL | 125 mg |  | 3.1 mL
70 | 154 | 70 mg |  | 1.75 mL | 116 mg |  | 2.9 mL
65 | 143 | 65 mg |  | 1.6 mL | 108 mg |  | 2.7 mL
60 | 132 | 60 mg |  | 1.5 mL | 100 mg |  | 2.5 mL
55 | 121 | 55 mg |  | 1.4 mL | 91 mg |  | 2.25 mL
50 | 110 | 50 mg |  | 1.25 mL | 83 mg |  | 2.1 mL
45 | 99 | 45 mg |  | 1.1 mL | 75 mg |  | 1.9 mL
40 | 88 | 40 mg |  | 1 mL | 66 mg |  | 1.6 mL

Pediatric Patients (Greater Than 1 Week of Age)

6 to 7.5 mg/kg/day in 3 or 4 equally divided doses (2 to 2.5 mg/kg every 8 hours or 1.5 to 1.89 mg/kg every 6 hours).

Premature or Full-Term Neonates 1 Week of Age or Less

Up to 4 mg/kg/day may be administered in 2 equal doses every 12 hours.

It is desirable to limit treatment to a short term. The usual duration of treatment is 7 to 10 days. A longer course of therapy may be necessary in difficult and complicated infections. In such cases, monitoring of renal, auditory, and vestibular functions is advised, because neurotoxicity is more likely to occur when treatment is extended longer than 10 days.

Dosage in Patients with Cystic Fibrosis

In patients with cystic fibrosis, altered pharmacokinetics may result in reduced serum concentrations of aminoglycosides. Measurement of tobramycin serum concentration during treatment is especially important as a basis for determining appropriate dose. In patients with severe cystic fibrosis, an initial dosage regimen of 10 mg/kg/day in 4 equally divided doses is recommended. This dosing regimen is suggested only as a guide. The serum levels of tobramycin should be measured directly during treatment due to wide interpatient variability.

Administration for Patients with Impaired Renal Function

Whenever possible, serum tobramycin concentrations should be monitored during therapy.

Following a loading dose of 1 mg/kg, subsequent dosage in these patients must be adjusted, either with reduced doses administered at 8-hour intervals or with normal doses given at prolonged intervals. Both of these methods are suggested as guides to be used when serum levels of tobramycin cannot be measured directly. They are based on either the creatinine clearance or the serum creatinine of the patient because these values correlate with the half-life of tobramycin. The dosage schedule derived from either method should be used in conjunction with careful clinical and laboratory observations of the patient and should be modified as necessary. Neither method should be used when dialysis is being performed.

Reduced Dosage at 8-Hour Intervals

When the creatinine clearance rate is 70 mL or less per minute or when the serum creatinine value is known, the amount of the reduced dose can be determined by multiplying the normal dose from Table 3by the percent of normal dose from the accompanying nomogram.

An alternate rough guide for determining reduced dosage at 8-hour intervals (for patients whose steady-state serum creatinine values are known) is to divide the normally recommended dose by the patient’s serum creatinine.

Normal Dosage at Prolonged Intervals

If the creatinine clearance rate is not available and the patient’s condition is stable, a dosage frequency in hoursfor the dosage given in Table 3can be determined by multiplying the patient’s serum creatinine by 6.

Dosage in Obese Patients

The appropriate dose may be calculated by using the patient’s estimated lean body weight plus 40% of the excess as the basic weight on which to figure mg/kg.

Intravenous Administration

For intravenous administration, the usual volume of diluent (0.9% Sodium Chloride Injection or 5% Dextrose Injection) is 50 to 100 mL for adult doses. For pediatric patients, the volume of diluent should be proportionately less than for adults. The diluted solution usually should be infused over a period of 20 to 60 minutes. Infusion periods of less than 20 minutes are not recommended because peak serum levels may exceed 12 mcg/mL (see Warningsbox).

Tobramycin for Injection, USP should not be physically premixed with other drugs but should be administered separately according to the recommended dose and route.

Parenteral drug products should be inspected visually for particulate matter and discoloration prior to administration, whenever solution and container permit.

Directions for Proper Use of Pharmacy Bulk Package

Use Aseptic Technique – Not for Direct Infusion

The pharmacy bulk package is for use in a Pharmacy Admixture Service only.

1. During use, container must be stored and all manipulations performed in an appropriate laminar flow hood.
2. Remove cover from container and cleanse closure with antiseptic.
3. A single entry through the vial closure should be made with a sterile dispensing set which allows measured dispensing of the contents. Transfer individual dose(s) to appropriate intravenous infusion solutions without delay. Use of a syringe with needle is not recommended as it may cause leakage. Multiple entries will also increase the potential of microbial and particulate contamination. The above process should be carried out under a laminar flow hood using aseptic technique. ANY UNUSED PORTION MUST BE DISCARDED WITHIN 4 HOURS.
4. Parenteral drug products should be inspected visually for particulate matter and discoloration prior to administration, whenever solution and container permit.

HOW SUPPLIED

Tobramycin for Injection, USP Pharmacy Bulk Package, containing tobramycin sulfate equivalent to 1.2 g of tobramycin (dry powder) and is available as:

NDC No. | Units per Carton | Tobramycin Content
70436-110-36 | Not saleable unit | 1.2 g
70436-110-80 | 1 vial per carton | 1.2 g per vial
70436-110-56 | 6 vials per carton | 1.2 g per vial

Store at 20° to 25°C (68° to 77°F) [See USP Controlled Room Temperature].

Manufactured by: Hainan Poly Pharm. Co., Ltd., Guilinyang Economic Development Zone, Haikou, Hainan, China 571127

Distributed by: Slate Run Pharmaceuticals, LLC Columbus, Ohio 43215

10000247/02

Revised 09/2023

PACKAGE/LABEL PRINCIPAL DISPLAY PANEL

NDC 70436-110-36

Tobramycin for Injection, USP